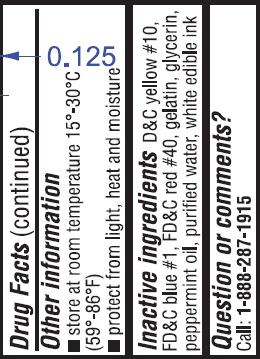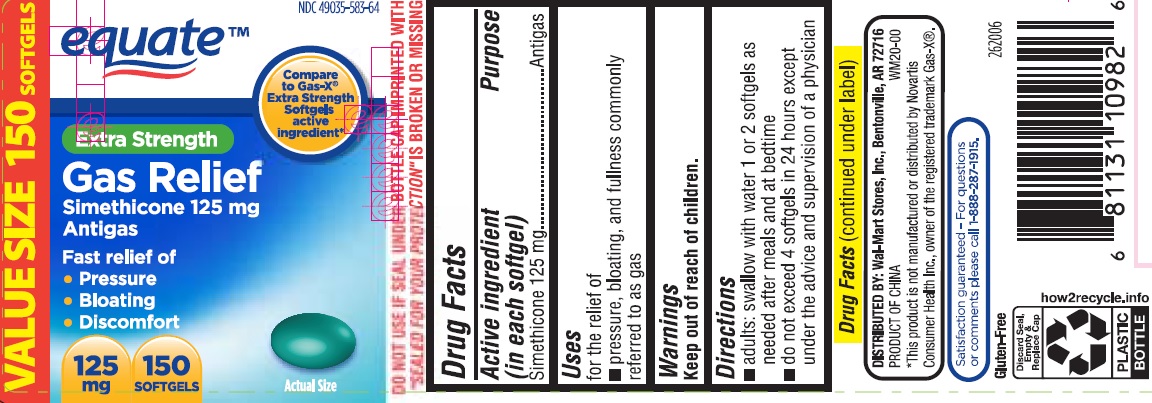 DRUG LABEL: Gas Relief
NDC: 49035-583 | Form: CAPSULE, LIQUID FILLED
Manufacturer: Wal-Mart Stores Inc
Category: otc | Type: HUMAN OTC DRUG LABEL
Date: 20241121

ACTIVE INGREDIENTS: DIMETHICONE 125 mg/1 1
INACTIVE INGREDIENTS: D&C YELLOW NO. 10; FD&C BLUE NO. 1; FD&C RED NO. 40; GELATIN; GLYCERIN; PEPPERMINT OIL; WATER

EXTRA STRENGTH GAS RELIEF

Drug Facts

Active ingredient (in each softgel)

Simethicone 125 mg

Purpose

Antigas

Uses

for the relief of

- pressure, bloating, and fullness commonly referred to as gas

Warnings

Keep out of reach of children.

Directions

- adults: swallow with water 1 or 2 softgels as needed after meals and at bedtime
- do not exceed 4 softgels in 24 hours except under the advice and supervision of a physician

Other information

- store at room temperature 15°-30°C (59°-86°F)
- protect from light, heat and moisture

Inactive ingredients

D&C yellow #10, FD&C blue #1, FD&C red #40, gelatin, glycerin, peppermint oil, purified water, white edible ink

Questions or Comments?

Call: 1-888-287-1915

PRINCIPAL DISPLAY PANEL

EXTRA STRENGTH GAS RELIEF

ANTIGAS SIMETHICONE 125 mg 150 SOFTGELS

NDC 49035-583-64

*Compare to the active ingredient in Gas-X® Extra Strength Softgels